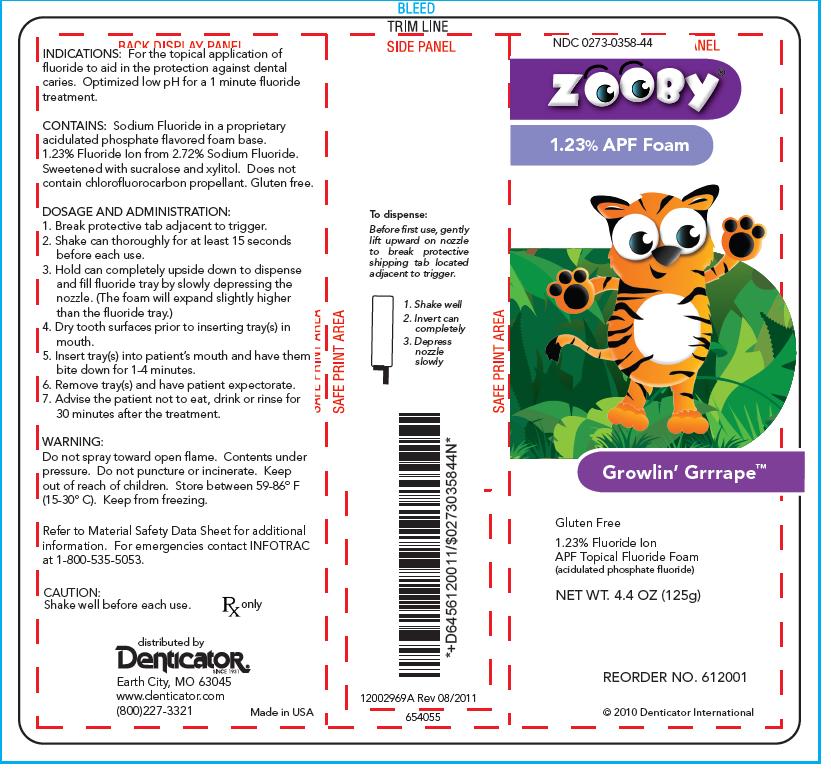 DRUG LABEL: ZOOBY

NDC: 0273-0358 | Form: AEROSOL, FOAM
Manufacturer: Young Dental Manufacturing Co 1, LLC
Category: prescription | Type: HUMAN PRESCRIPTION DRUG LABEL
Date: 20230103

ACTIVE INGREDIENTS: SODIUM FLUORIDE 2.72 g/100 g

Description

Product Name- ZOOBY, 1.23 % APF Foam (Growlin Grrrape Flavor)

Distributed By - Denticator Earth City, MO 63045.

Net Weight - 4.4 OZ (125g)

RX Only

ZOOBY, 1.23 % APF Foam (Growlin Grrrape Flavor) contains 1.23 % Fluoride Ion from 2.72 % Sodium Fluoride. The Product is free from Does not contain chlorofluorocarbon propellant. Gluten free.

Indications

For the topical application of fluoride to aid in the protection against dental caries. Optimized low pH for a 1 minute fluoride treatments.

Dosage and Administration

1. Break protective tab adjacent to trigger.

2. Shake can thoroughly for at least 15 seconds before each use.

3. Hold can completely upside down to dispense and fill fluoride tray by slowly depressing the nozzle. (The foam will expand slightly higher than the fluoride tray.)

4. Dry tooth surfaces prior to inserting tray(s) in mouth.

5. Insert tray(s) into patient’s mouth and have them bite down for 1-4 minutes.

6. Remove tray(s) and have patient expectorate.

7. Advise the patient not to eat, drink or rinse for 30 minutes after the treatment.

Warnings

Do not spray toward open flame. Contents under pressure. Do not puncture or incinerate. Keep out of reach of children. Store between 59-86º F (15-30º C). Keep from freezing.

Refer to Material Safety Data Sheet for additional information. For emergencies contact INFOTRAC at 1-800-535-5053

Product Label

Product Label of 1.23 % APF Foam (Growlin Grrrape)